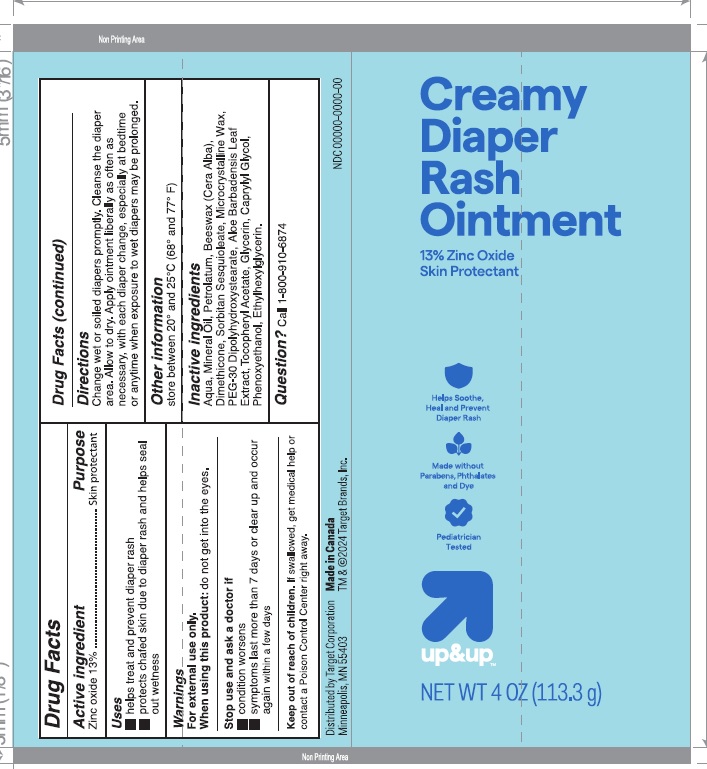 DRUG LABEL: Creamy Diaper Rash
NDC: 42669-013 | Form: OINTMENT
Manufacturer: Davion, Inc
Category: otc | Type: HUMAN OTC DRUG LABEL
Date: 20251229

ACTIVE INGREDIENTS: ZINC OXIDE 13 g/100 g
INACTIVE INGREDIENTS: CAPRYLYL GLYCOL; PHENOXYETHANOL; WATER; MINERAL OIL; PETROLATUM; YELLOW WAX; DIMETHICONE; SORBITAN SESQUIOLEATE; MICROCRYSTALLINE WAX; PEG-30 DIPOLYHYDROXYSTEARATE; ALOE VERA LEAF; .ALPHA.-TOCOPHEROL ACETATE; GLYCERIN; ETHYLHEXYLGLYCERIN

Active Ingredients

Zinc Oxide 13%

Purpose

Skin Protectant

Uses

- helps treat and prevent diaper rash
- protects chafed skin due to diaper rash and helps seal out wetness

Warnings

For external use only

When using this product

do not get into eyes

Stop use and ask a doctor if

- condition worsens
- symptoms last more than 7 days or clear up and occur again within a few days

Keep out of reach of children

If swallowed, get medical help or contact a Poison Control Center right away.

Directions

- Change wet or soiled diapers promptly
- Cleanse the diaper area.
- Allow to dry
- Apply cream liberally as often as necessary, with each diaper change, especially at bedtime or anytime when exposure to wet diapers may be prolonged

Other information

store between 20° and 25°C (68° to 77°F)

Inactive ingredients

Aqua, Mineral Oil, Petrolatum, Beeswax (Cera Alba), Dimethicone, Sorbitan Sesquioleate, Microcrystalline Wax, PEG-30 Dipolyhydroxystearate, Aloe Barbadensis Leaf Extract, Tocopheryl Acetate, Glycerin, Caprylyl Glycol, Phenoxyethanol, Ethylhexylglycerin.

Questions?

Call 1-800-910-6874

Distributed by:

Target Corporation

Minneapolis, MN 55403

Made in Canada

TM & © 2024 Target Brands, Inc

PRINCIPAL DISPLAY PANEL

Creamy Diaper Rash Ointment

13% Zinc Oxide

Skin Protectant

Helps Soothe, Heel and Prevent Diaper Rash

Made without Parabens, Pthalates and Dye

Pediatrician Tested

up&up

NET WT 4 OZ (113.3 g)